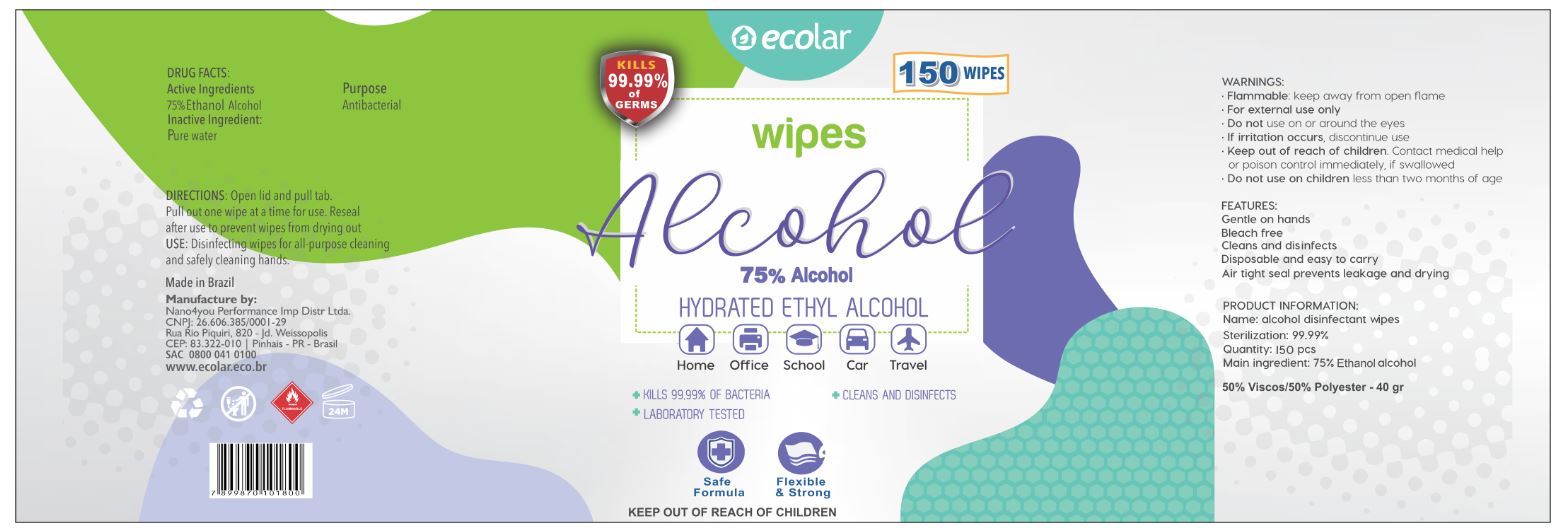 DRUG LABEL: Alcohol Wipes
NDC: 79816-001 | Form: CLOTH
Manufacturer: Nano4you Performance Importacao E Distribuicao LTDA
Category: otc | Type: HUMAN OTC DRUG LABEL
Date: 20201106

ACTIVE INGREDIENTS: ALCOHOL 0.75 mL/1 mL
INACTIVE INGREDIENTS: WATER

Alcohol Wipes

Active Ingredients

75% Ethanol Alcohol

Purpose

Antibacterial

Inactive Ingredient:

pure water

DIRECTIONS:

Open lid and pull tab. Pull out one wipe at a time for use. Reseal after use to prevent wipes from drying out

USE:

Disinfecting wipes for all-purpose cleaning and safely cleaning hands.

WARNINGS:

- Flammable:keep away from open flame
- For external use only

Do not use

- on or around the eyes
- If irritation occurs, discontinue use

Keep out of reach of children.

- Contact medical help or poison control immediately, if swallowed
- Do not use on children less than two months of age